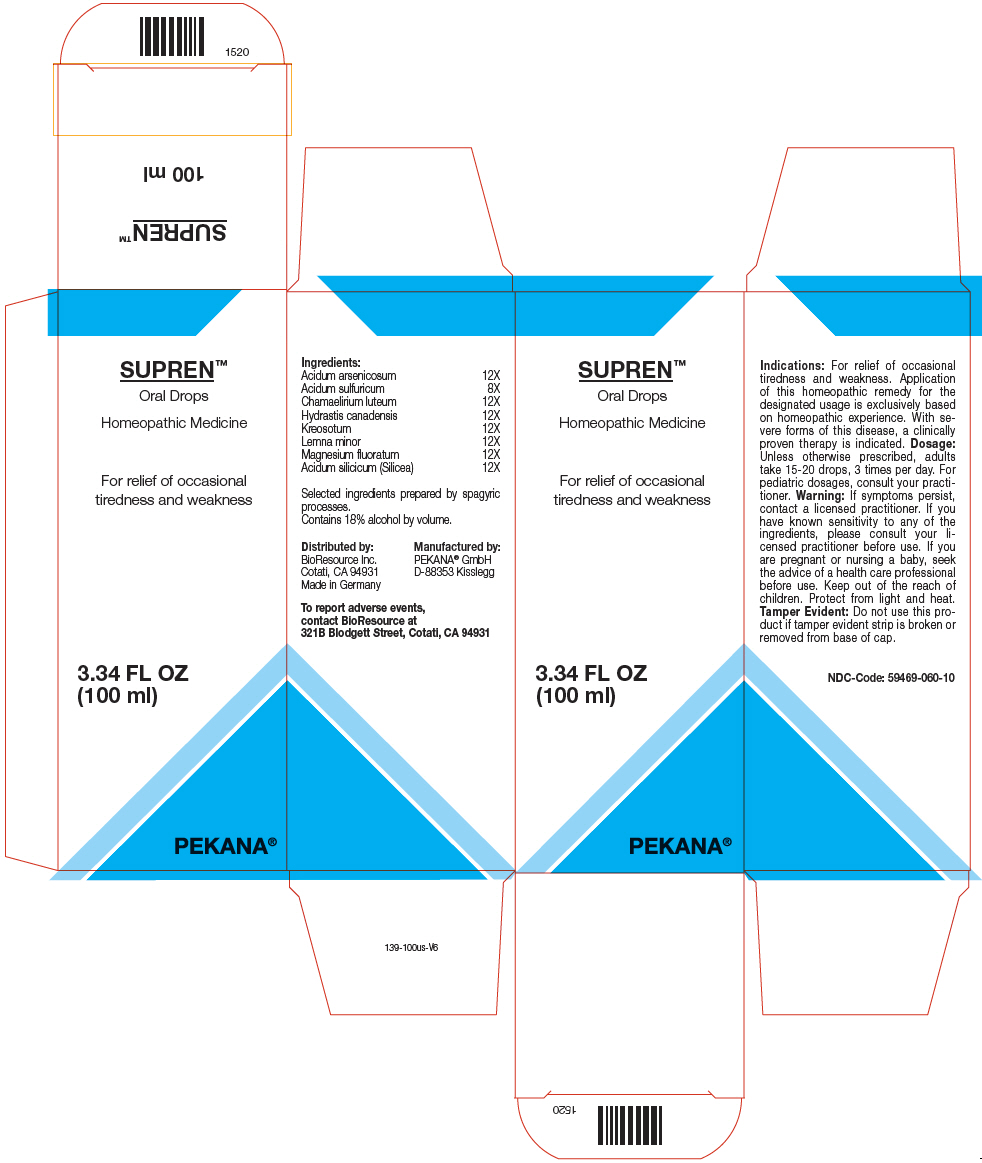 DRUG LABEL: SUPREN
NDC: 59469-060 | Form: SOLUTION/ DROPS
Manufacturer: PEKANA Naturheilmittel GmbH
Category: homeopathic | Type: HUMAN OTC DRUG LABEL
Date: 20221222

ACTIVE INGREDIENTS: Arsenic Trioxide 12 [hp_X]/100 mL; Sulfuric Acid 8 [hp_X]/100 mL; Chamaelirium luteum Root 12 [hp_X]/100 mL; Goldenseal 12 [hp_X]/100 mL; Wood Creosote 12 [hp_X]/100 mL; LEMNA MINOR WHOLE 12 [hp_X]/100 mL; Magnesium fluoride 12 [hp_X]/100 mL; Silicon Dioxide 12 [hp_X]/100 mL
INACTIVE INGREDIENTS: Water; Alcohol

SUPREN™

ACTIVE INGREDIENT

Ingredients:
Acidum arsenicosum | 12X
Acidum sulfuricum | 8X
Chamaelirium luteum | 12X
Hydrastis canadensis | 12X
Kreosotum | 12X
Lemna minor | 12X
Magnesium fluoratum | 12X
Acidum silicicum (Silicea) | 12X

Selected ingredients prepared by spagyric processes.

INACTIVE INGREDIENT

Contains 18% alcohol by volume.

Indications

PURPOSE

For relief of occasional tiredness and weakness. Application of this homeopathic remedy for the designated usage is exclusively based on homeopathic experience. With severe forms of this disease, a clinically proven therapy is indicated.

Dosage

Unless otherwise prescribed, adults take 15-20 drops, 3 times per day. For pediatric dosages, consult your practitioner.

Warning

If symptoms persist, contact a licensed practitioner. If you have known sensitivity to any of the ingredients, please consult your licensed practitioner before use. If you are pregnant or nursing a baby, seek the advice of a health care professional before use.

Keep out of the reach of children.

STORAGE AND HANDLING

Protect from light and heat.

Tamper Evident

Do not use this product if tamper evident strip is broken or removed from base of cap.

QUESTIONS

To report adverse events, contact BioResource at 321B Blodgett Street, Cotati, CA 94931

Distributed by:
BioResource Inc.
Cotati, CA 94931

Manufactured by:
PEKANA® GmbH
D-88353 Kisslegg

PRINCIPAL DISPLAY PANEL - 100 ml Bottle Box

SUPREN™
Oral Drops

Homeopathic Medicine

For relief of occasional
tiredness and weakness

3.34 FL OZ
(100 ml)

PEKANA®